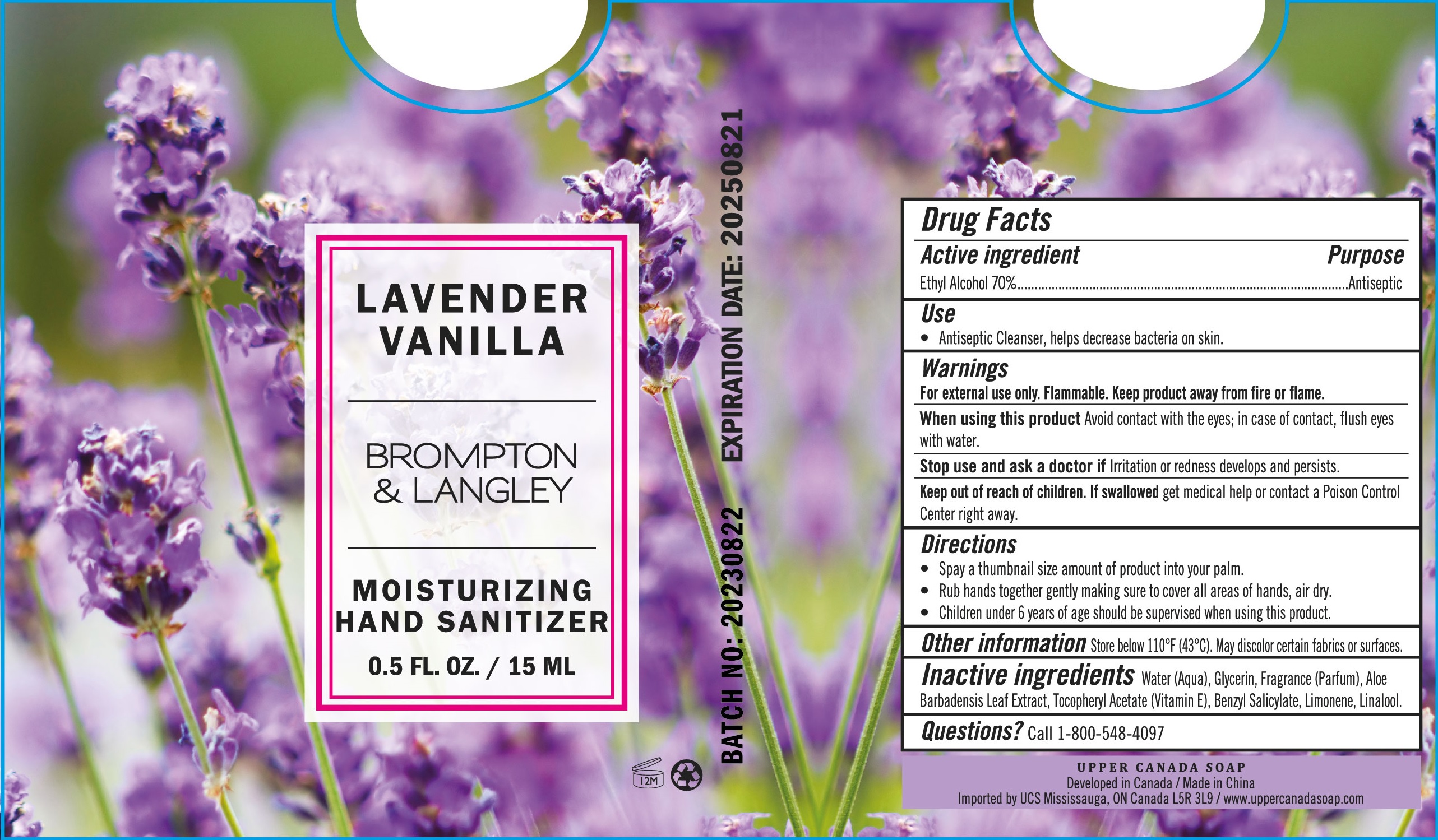 DRUG LABEL: Brompton and Langley Moisturizing Hand Sanitizer Lavnder Vanilla
NDC: 56136-730 | Form: GEL
Manufacturer: Ganzhou Olivee Cosmetic Co., Ltd.
Category: otc | Type: HUMAN OTC DRUG LABEL
Date: 20231019

ACTIVE INGREDIENTS: ALCOHOL 70 mL/100 mL
INACTIVE INGREDIENTS: WATER; GLYCERIN; BENZYL SALICYLATE; .ALPHA.-TOCOPHEROL ACETATE, D-; ALOE VERA LEAF

HAND SANITIZER

Active ingredient

Ethyl Alcohol 70%

Purpose

Antiseptic

Use

Antiseptic Cleanser, helps decrease bacteria on skin.

Warnings

For external use only.

Flammable. Keep product away from fire or flame.

When using this product avoid contact with eyes. In case of contact flush eyes with water.

Stop use and ask a doctor if irritation orredness develops and persists.

Keep out of reach of children.

If swallowed, get medical help or contact a Poison Control Center right away.

Directions

- Spray a thumbnail size amount of product into your palm.
- Rub hands together gently making sure to cover all areas of hands, air dry.
- Children under 6 years of age should be supervised when using this product.

Inactive ingredients

Water (Aqua), Glycerin, Fragrance (Parfum), Aloe Barbadensis leaf Extract, Tocopheryl Acetate (Vitamin E), Benzyl Salicylate, Limonene, Linalool.